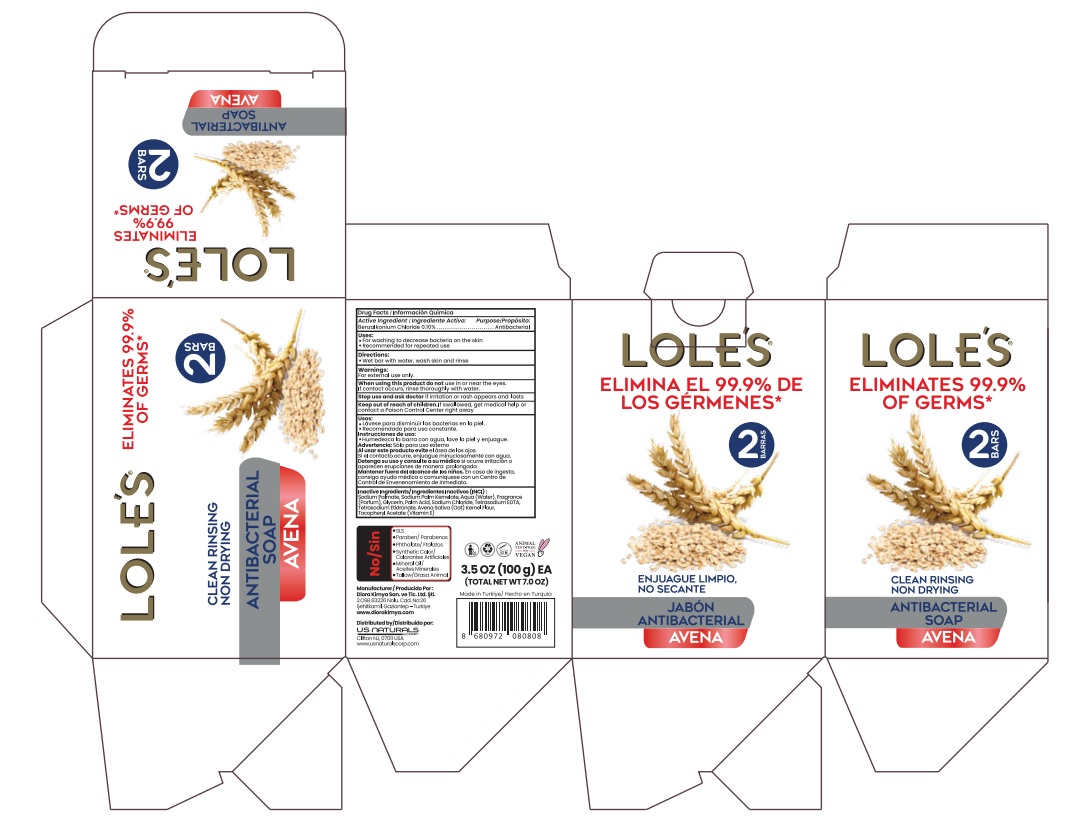 DRUG LABEL: LOLES
NDC: 73485-004 | Form: SOAP
Manufacturer: Diora Kimya Sanayi ve Ticaret Limited Sirketi
Category: otc | Type: HUMAN OTC DRUG LABEL
Date: 20221201

ACTIVE INGREDIENTS: BENZALKONIUM CHLORIDE 0.1 g/100 g
INACTIVE INGREDIENTS: ALPHA-TOCOPHEROL ACETATE 0.02 g/100 g; SODIUM PALMATE 65 g/100 g; WATER 15 g/100 g; SODIUM PALM KERNELATE 16 g/100 g; GLYCERIN 1.5 g/100 g; EDETATE SODIUM 0.02 g/100 g; SODIUM CHLORIDE 0.48 g/100 g; ETIDRONATE TETRASODIUM 0.02 g/100 g; FRAGRANCE 13576 0.86 g/100 g; PALM ACID 0.5 g/100 g; AVENA SATIVA LEAF 0.5 g/100 g

Antibacterial Bar Soap for Personal Use

ACTIVE INGREDIENT

Benzalkonium Chloride........0.10%

PURPOSE

Antimicrobial. Antibacterial Bar Soap.

INDICATIONS AND USAGE

- For washing to decrease bacteria on the skin
- Recommended for repeated use

WARNINGS

For external use only.

When using this product, do not use in or near the eyes. If contact occurs, rinse thorougly with water.

Stop use and ask doctor if irritation or rash appears and lasts.

Keep out of reach of children. if swallowed, get medical help or contact a Poison Control Center right away.

DOSAGE AND ADMINISTRATION

- Wet bar with water, wash skin and rinse

INACTIVE INGREDIENT

Sodium Palmate, Sodium Palm Kernelate, Aqua (Water), Fragrance (Parfum), Glycerin, Palm Acid, Sodium Chloride, Tetrasodium EDTA, Tetrasodium Etidronate, Avena Sativa (Oat) Kernel Flour, Tocopheryl Acetate (Vitamin E)